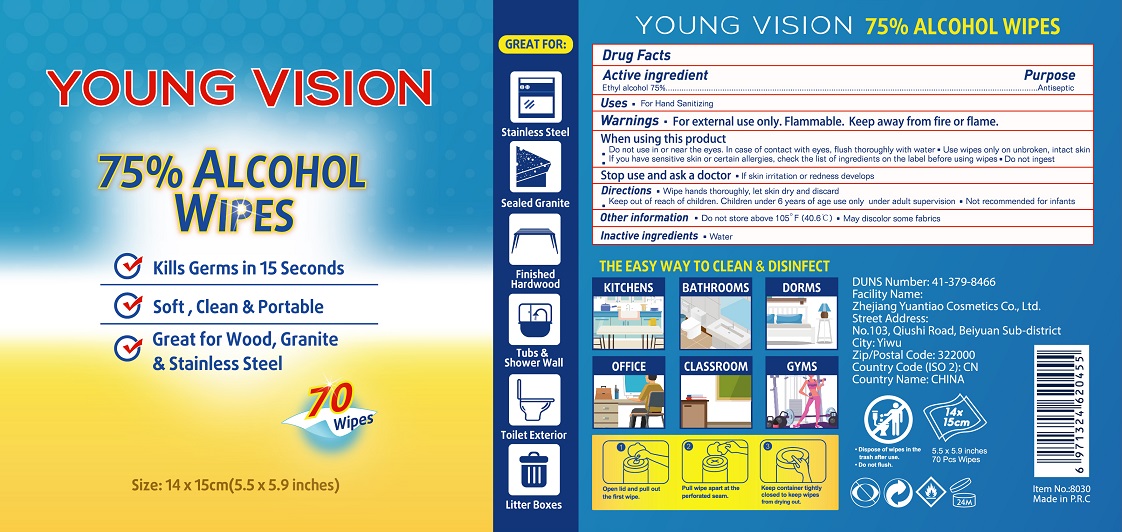 DRUG LABEL: Alcohol Wipes
NDC: 74737-2101 | Form: CLOTH
Manufacturer: Zhejiang Yuantiao Cosmetics Co., Ltd.
Category: otc | Type: HUMAN OTC DRUG LABEL
Date: 20200709

ACTIVE INGREDIENTS: ALCOHOL 3 mL/1 1
INACTIVE INGREDIENTS: WATER

YuanTiao, Alcohol wipes, 75% Alcohol

Active ingredient

Ethyl alcohol 75% v/v. Purpose: Antiseptic

Purpose

Antiseptic

When Using this product

- Do not use in or near the eyes. In case of contact with eyes, flush throughly with water.
- Use wipes only on unbroken, intact skin.
- If you have sensitive skin or certain allergies, chek the list of ingredients on the label before using wipes.
- Don not ingest.

Do not use in or near the eyes.

Stop use and ask a doctor

- If skin irritation or redness develops.

Keep out of reach of children.

Children under 6 years of age use only under adult supervision.

Not recommended for infants.

Uses

- For Hand Sanitizing

Directions

- Wipe hands thoroughly, let skin dry and discard.
- Keep out of reach of children. Children under 6 years of age use only under adult supervision.
- Not recommended for infants.

Warnings

- For external use only. Flammable. Keep away from fire or flame.

Other information

- Do not store above 105℉ (40.6℃)
- May discolor some fabrics

Inactive ingredients

- Water